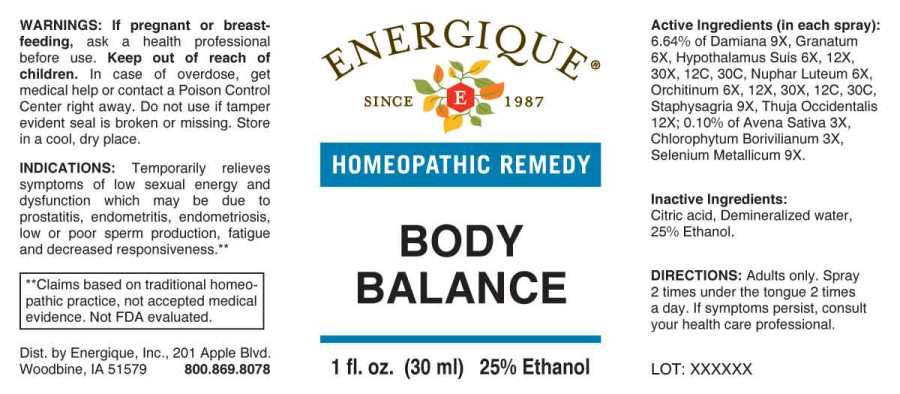 DRUG LABEL: Body Balance
NDC: 44911-0635 | Form: SPRAY
Manufacturer: Energique, Inc.
Category: homeopathic | Type: HUMAN OTC DRUG LABEL
Date: 20240214

ACTIVE INGREDIENTS: AVENA SATIVA FLOWERING TOP 3 [hp_X]/1 mL; CHLOROPHYTUM BORIVILIANUM WHOLE 3 [hp_X]/1 mL; PUNICA GRANATUM ROOT BARK 6 [hp_X]/1 mL; NUPHAR LUTEA ROOT 6 [hp_X]/1 mL; BOS TAURUS HYPOTHALAMUS 6 [hp_X]/1 mL; SUS SCROFA TESTICLE 6 [hp_X]/1 mL; TURNERA DIFFUSA LEAFY TWIG 9 [hp_X]/1 mL; SELENIUM 9 [hp_X]/1 mL; DELPHINIUM STAPHISAGRIA SEED 9 [hp_X]/1 mL; THUJA OCCIDENTALIS LEAFY TWIG 12 [hp_X]/1 mL
INACTIVE INGREDIENTS: CITRIC ACID MONOHYDRATE; WATER; ALCOHOL

DRUG FACTS:

ACTIVE INGREDIENTS:

(in each spray): 6.64% of Damiana 9X, Granatum 6X, Hypothalamus Suis 6X, 12X, 30X, 12C, 30C, Nuphar Luteum 6X, Orchitinum (Suis) 6X, 12X, 30X, 12C, 30C, Staphysagria 9X, Thuja Occidentalis 12X;0.10% of Avena Sativa 3X, Chlorophytum Borivilianum 3X, Selenium Metallicum 9X.

INDICATIONS:

Temporarily relieves symptoms of low sexual energy and dysfunction which may be due to prostatitis, endometritis, endometriosis, low or poor sperm production, fatigue and decreased responsiveness.**

**Claims based on traditional homeopathic practice, not accepted medical evidence. Not FDA evaluated.

WARNINGS:

If pregnant or breast-feeding, ask a health professional before use. Keep out of reach of children. In case of overdose, get medical help or contact a Poison Control Center right away. Do not use if tamper evident seal is broken or missing. Store in a cool, dry place.

KEEP OUT OF REACH OF CHILDREN:

In case of overdose, get medical help or contact a Poison Control Center right away.

DIRECTIONS:

Adults only. Spray 2 times under the tongue 2 times a day. If symptoms persist, consult your health care professional.

INDICATIONS:

Temporarily relieves symptoms of low sexual energy and dysfunction which may be due to prostatitis, endometritis, endometriosis, low or poor sperm production, fatigue and decreased responsiveness.**

**Claims based on traditional homeopathic practice, not accepted medical evidence. Not FDA evaluated.

INACTIVE INGREDIENTS:

Citric acid, Demineralized water, 25% Ethanol.

QUESTIONS:

Dist. by Energique, Inc.

201 Apple Blvd.

Woodbine, IA 51579 800.869.8078

PACKAGE DISPLAY LABEL:

ENERGIQUE

SINCE 1987

HOMEOPATHIC REMEDY

BODY BALANCE

1 fl. oz. (30 ml)